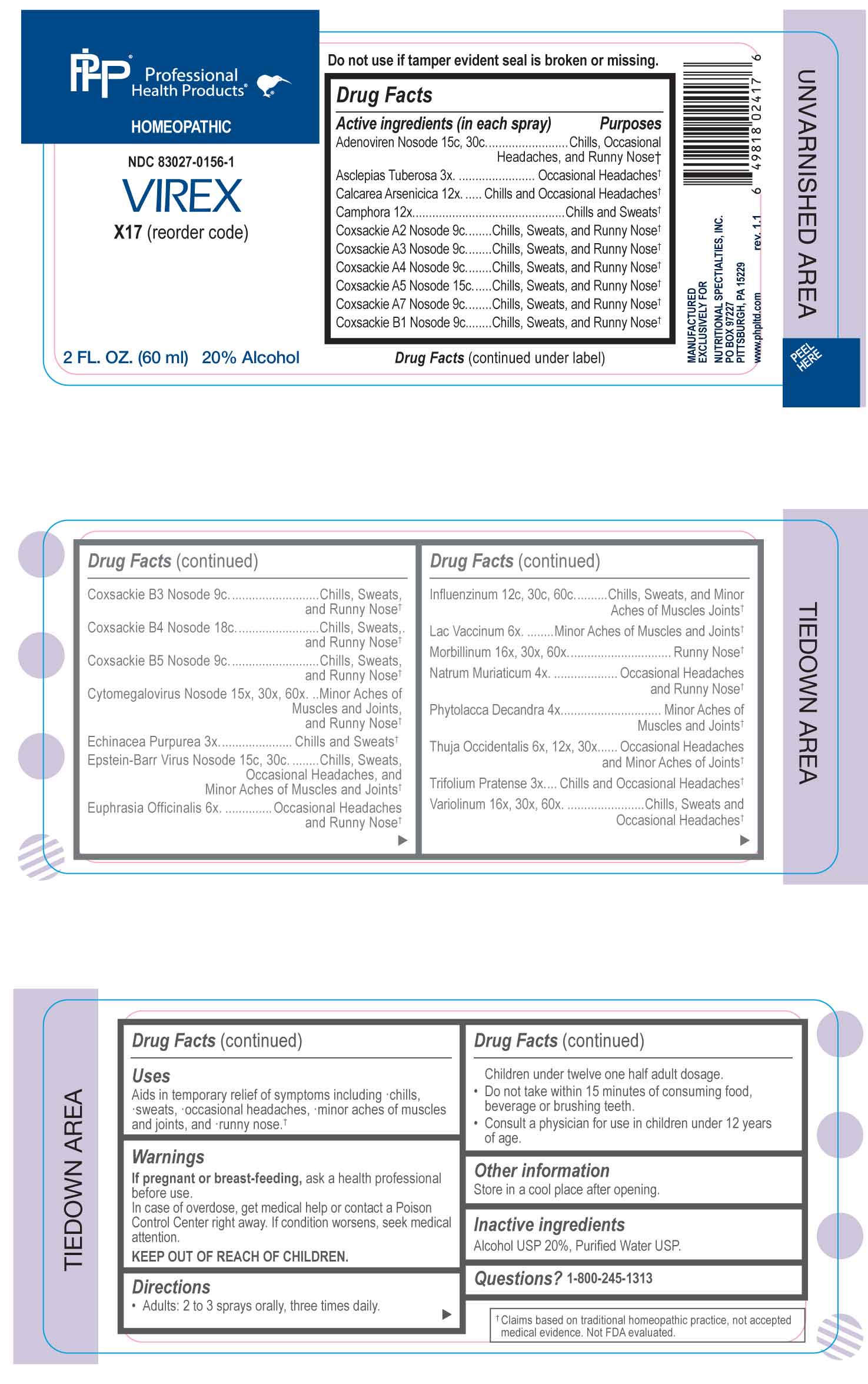 DRUG LABEL: Virex
NDC: 83027-0156 | Form: SPRAY
Manufacturer: Nutritional Specialties, Inc.
Category: homeopathic | Type: HUMAN OTC DRUG LABEL
Date: 20251003

ACTIVE INGREDIENTS: ASCLEPIAS TUBEROSA ROOT 3 [hp_X]/1 mL; ECHINACEA PURPUREA WHOLE 3 [hp_X]/1 mL; TRIFOLIUM PRATENSE FLOWER 3 [hp_X]/1 mL; SODIUM CHLORIDE 4 [hp_X]/1 mL; PHYTOLACCA AMERICANA ROOT 4 [hp_X]/1 mL; EUPHRASIA STRICTA 6 [hp_X]/1 mL; COW MILK 6 [hp_X]/1 mL; THUJA OCCIDENTALIS LEAFY TWIG 6 [hp_X]/1 mL; CALCIUM ARSENATE 12 [hp_X]/1 mL; CAMPHOR (NATURAL) 12 [hp_X]/1 mL; INFLUENZA A VIRUS A/VICTORIA/4897/2022 IVR-238 (H1N1) ANTIGEN (FORMALDEHYDE INACTIVATED) 12 [hp_C]/1 mL; INFLUENZA A VIRUS A/THAILAND/8/2022 IVR-237 (H3N2) ANTIGEN (FORMALDEHYDE INACTIVATED) 12 [hp_C]/1 mL; INFLUENZA B VIRUS B/AUSTRIA/1359417/2021 BVR-26 WHOLE 12 [hp_C]/1 mL; INFLUENZA B VIRUS B/PHUKET/3073/2013 BVR-1B WHOLE 12 [hp_C]/1 mL; HUMAN HERPESVIRUS 5 15 [hp_X]/1 mL; MEASLES VIRUS 16 [hp_X]/1 mL; VARIOLA VIRUS 16 [hp_X]/1 mL; HUMAN COXSACKIEVIRUS A2 9 [hp_C]/1 mL; HUMAN COXSACKIEVIRUS A 9 [hp_C]/1 mL; HUMAN COXSACKIEVIRUS A7 9 [hp_C]/1 mL; HUMAN COXSACKIEVIRUS B1 9 [hp_C]/1 mL; HUMAN COXSACKIEVIRUS B3 9 [hp_C]/1 mL; HUMAN COXSACKIEVIRUS B5 9 [hp_C]/1 mL; HUMAN ADENOVIRUS E SEROTYPE 4 STRAIN CL-68578 ANTIGEN 15 [hp_C]/1 mL; HUMAN HERPESVIRUS 4 15 [hp_C]/1 mL; HUMAN COXSACKIEVIRUS B 18 [hp_C]/1 mL
INACTIVE INGREDIENTS: WATER; ALCOHOL

DRUG FACTS:

ACTIVE INGREDIENTS:

Adenoviren Nosode 15C, 30C, Asclepias Tuberosa 3X, Calcarea Arsenicica 12X, Camphora 12X, Coxsackie A2 Nosode 9C, Coxsackie A3 Nosode 9C, Coxsackie A4 Nosode 9C, Coxsackie A5 Nosode 15C, Coxsackie A7 Nosode 9C, Coxsackie B1 Nosode 9C, Coxsackie B3 Nosode 9C, Coxsackie B4 Nosode 18C, Coxsackie B5 Nosode 9C, Cytomegalovirus Nosode 15X, 30X, 60X, Echinacea Purpurea 3X, Epstein-Barr Virus Nosode 15C, 30C, Euphrasia Officinalis 6X, Influenzinum 12C, 30C, 60C, Lac Vaccinum 6X, Morbillinum 16X, 30X, 60X, Natrum Muriaticum 4X, Phytolacca Decandra 4X, Thuja Occidentalis 6X, 12X, 30X, Trifolium Pratense 3X, Variolinum 16X, 30X, 60X.

PURPOSE:

Adenoviren Nosode – Chills, Occasional Headaches, and Runny Nose,† Asclepias Tuberosa – Occasional Headaches,† Calcarea Arsenicica – Chills and Occasional Headaches,† Camphora – Chills and Sweats,† Coxsackie A2 Nosode – Chills, Sweats, and Runny Nose,† Coxsackie A3 Nosode - Chills, Sweats, and Runny Nose,† Coxsackie A4 Nosode - Chills, Sweats, and Runny Nose,† Coxsackie A5 Nosode - Chills, Sweats, and Runny Nose,† Coxsackie A7 Nosode - Chills, Sweats, and Runny Nose,† Coxsackie B1 Nosode - Chills, Sweats, and Runny Nose,† Coxsackie B3 Nosode - Chills, Sweats, and Runny Nose,† Coxsackie B4 Nosode - Chills, Sweats, and Runny Nose,† Coxsackie B5 Nosode - Chills, Sweats, and Runny Nose,† Cytomegalovirus Nosode – Minor Aches of Muscles and Joints, and Runny Nose,† Echinacea Purpurea – Chills and Sweats,† Epstein-Barr Virus Nosode – Chills, Sweats, Occasional Headaches, and Minor Aches of Muscles and Joints,† Euphrasia Officinalis – Occasional Headaches and Runny Nose,† Influenzinum – Chills, Sweats, and Minor Aches of Muscles and Joints,† Lac Vaccinum – Minor Aches of Muscles and Joints,† Morbillinum – Runny Nose,† Natrum Muriaticum – Occasional Headaches and Runny Nose,† Phytolacca Decandra – Minor Aches of Muscles and Joints,† Thuja Occidentalis – Occasional Headaches and Minor Aches of Joints,† Trifolium Pratense – Chills and Occasional Headaches,† Variolinum – Chills, Sweats and Occasional Headaches†

†Claims based on traditional homeopathic practice, not accepted medical evidence. Not FDA evaluated.

USES:

Aids in temporary relief of symptoms including chills, sweats, occasional headaches, minor aches of muscles and joints, and runny nose.

†Claims based on traditional homeopathic practice, not accepted medical evidence. Not FDA evaluated.

WARNINGS:

If pregnant or breast-feeding, ask a health professional before use.

In case of overdose, get medical help or contact a Poison Control Center right away.

If condition worsens, seek medical attention.

KEEP OUT OF REACH OF CHILDREN

Do not use if tamper evident seal is broken or missing.

Store in a cool place after opening

KEEP OUT OF REACH OF CHILDREN:

In case of overdose, get medical help or contact a Poison Control Center right away.

DIRECTIONS:

• Adults: 2 to 3 sprays orally, three times daily. Children under twelve one half adult dosage.

• Do not take within 15 minutes of consuming food, beverage or brushing teeth.

• Consult a physician for use in children under 12 years of age.

INACTIVE INGREDIENTS:

Alcohol USP 20%, Purified Water USP.

QUESTIONS:

MANUFACTURED EXCLUSIVELY FOR

NUTRITIONAL SPECIALTIES, INC.

PO BOX 97227

PITTSBURGH, PA 15229

www.phpitd.com

1-800-245-1313

PACKAGE LABEL DISPLAY:

Professional Health Products

NDC 83027-0156-1

VIREX

2 FL. OZ. (60 ml)